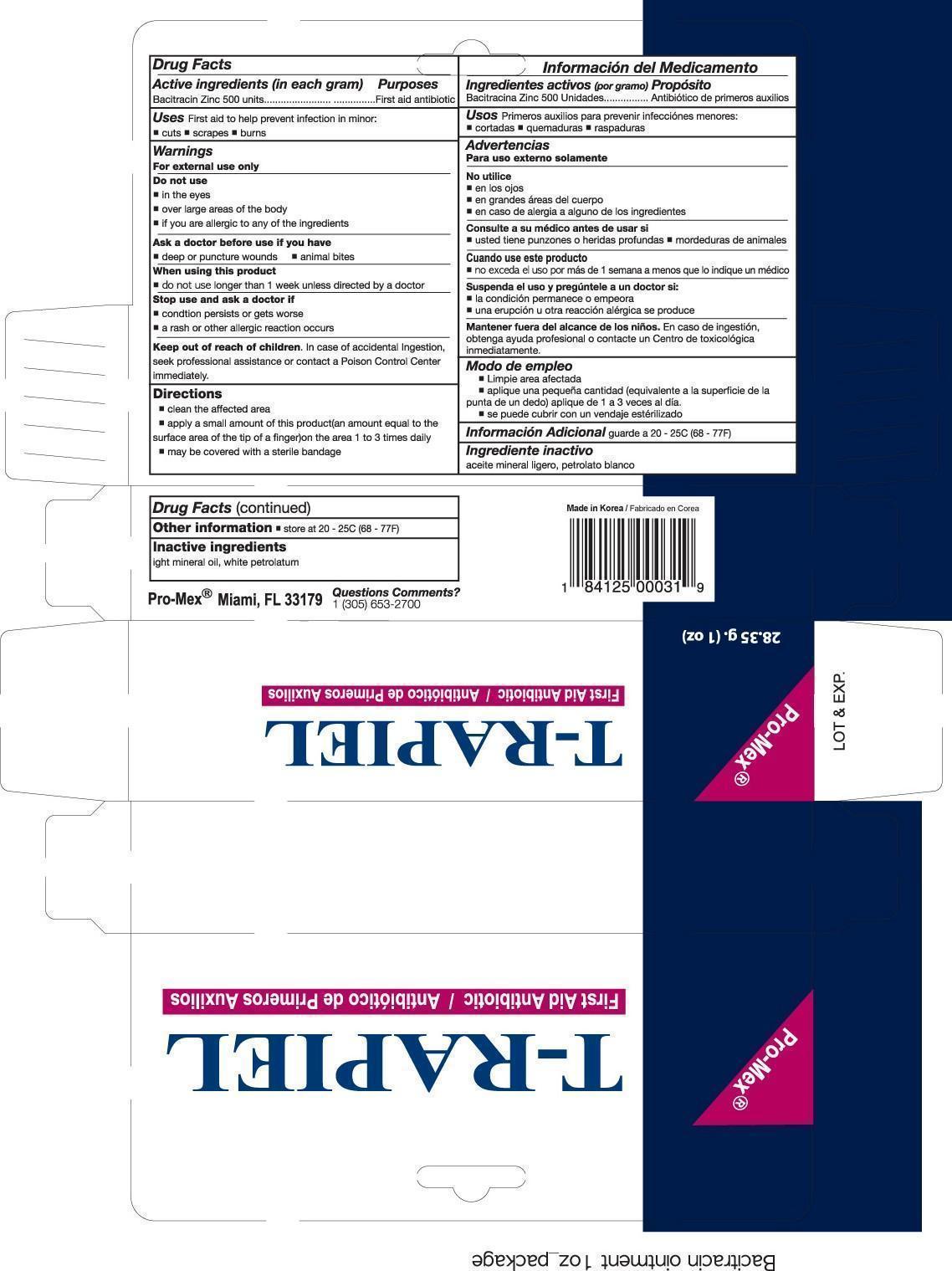 DRUG LABEL: Bacitracin Zinc
NDC: 58988-0031 | Form: OINTMENT
Manufacturer: Promex, LLC
Category: otc | Type: HUMAN OTC DRUG LABEL
Date: 20131210

ACTIVE INGREDIENTS: BACITRACIN ZINC 500 [USP'U]/1 g
INACTIVE INGREDIENTS: MINERAL OIL; PETROLATUM

Drug Facts

Active ingredient (in each gram)

Bacitracin Zinc 500 units

Purpose

First aid antibiotic

Uses

First aid to help prevent infection in minor:

- cuts
- scrapes
- burns

Warnings

For external use only

Do not use

- in the eyes
- over large areas of the body
- if you are allergic to any of the ingredients

Ask a doctor before use if you have

- deep or puncture wounds
- animal bites

When using this product

- do not use longer than 1 week unless directed by a doctor

Stop use and ask a doctor if

- condition persists or gets worse
- a rash or other allergic reaction develops

Keep out of reach of children

In case of accidental Ingestion, seek professional assistance or contact a Poison Control Center immediately.

Directions

- clean the affected area
- apply a small amount of this product (an amount equal to the surface area of the tip of a finger) on the area 1 to 3 times daily
- may be covered with a sterile bandage

Other information

store at 20 - 25C (68 - 77F)

Inactive ingredients

light mineral oil, white petrolatum